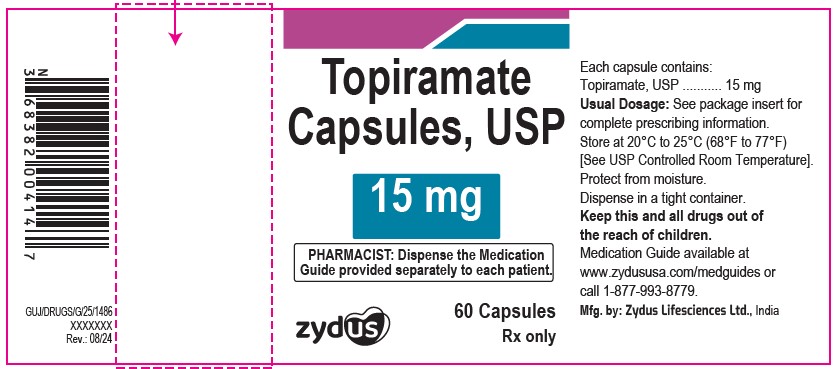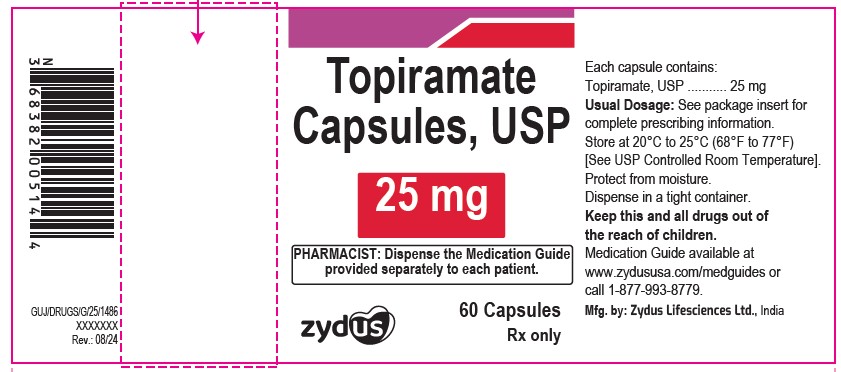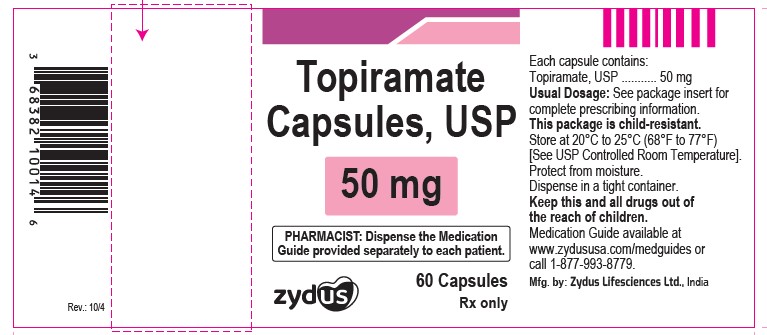 DRUG LABEL: topiramate
NDC: 65841-651 | Form: CAPSULE, COATED PELLETS
Manufacturer: Zydus Lifesciences Limited
Category: prescription | Type: HUMAN PRESCRIPTION DRUG LABEL
Date: 20241025

ACTIVE INGREDIENTS: TOPIRAMATE 15 mg/1 1
INACTIVE INGREDIENTS: HYPROMELLOSES; CELLULOSE ACETATE; GELATIN; POVIDONE; SODIUM LAURYL SULFATE; SUCROSE; TALC; TITANIUM DIOXIDE; WATER; FERROSOFERRIC OXIDE; POTASSIUM HYDROXIDE; PROPYLENE GLYCOL; SHELLAC

TOPIRAMATE TABLETS and TOPIRAMATE CAPSULES

PACKAGE LABEL.PRINCIPAL DISPLAY PANEL

NDC 65841-651-14 in bottle of 60 capsules

Topiramate Capsules USP, 15 mg

60 capsules

Rx only

NDC 65841-652-14 in bottle of 60 capsules

Topiramate Capsules USP, 25 mg

60 capsules

Rx only

NDC 65841-100-14 in bottle of 60 capsules

Topiramate Capsules USP, 50 mg

60 capsules

Rx only